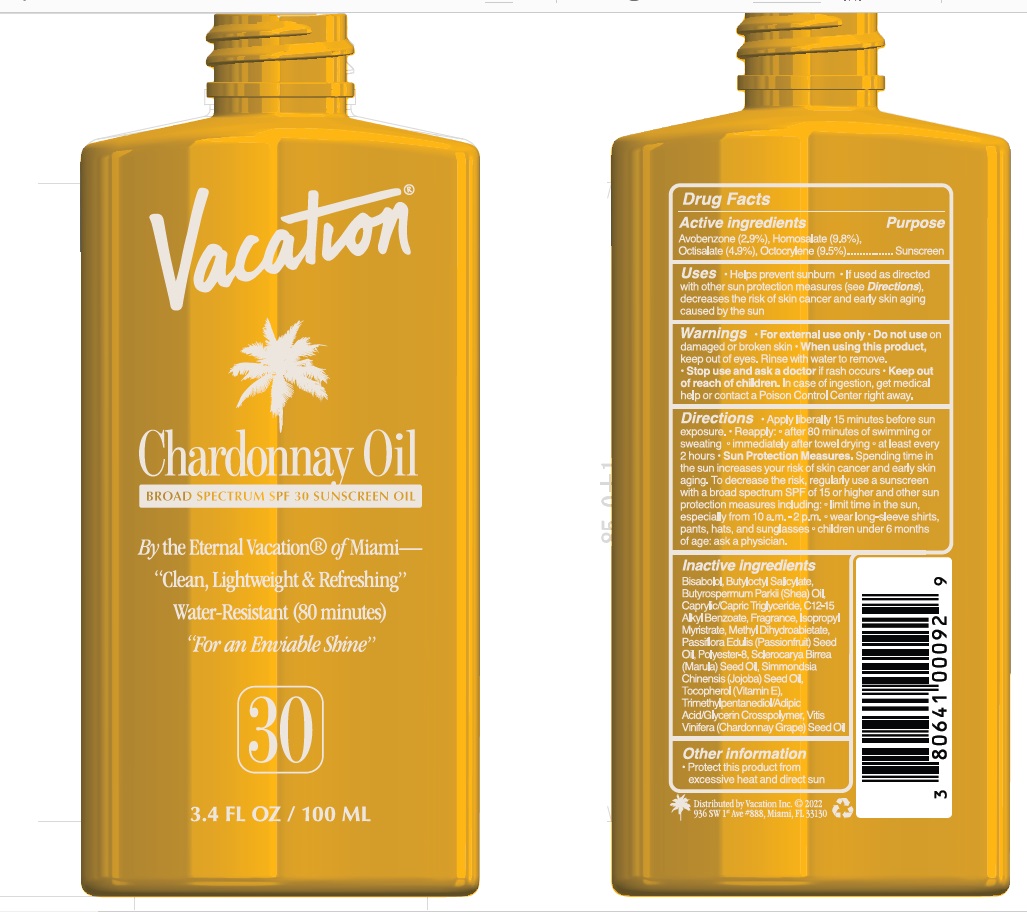 DRUG LABEL: Vacation SPF 30 Chardonnay Oil
NDC: 80641-008 | Form: OIL
Manufacturer: Vacation Inc.
Category: otc | Type: HUMAN OTC DRUG LABEL
Date: 20241220

ACTIVE INGREDIENTS: HOMOSALATE 9.8 g/100 mL; OCTISALATE 4.9 g/100 mL; AVOBENZONE 2.9 g/100 mL; OCTOCRYLENE 9.5 g/100 mL
INACTIVE INGREDIENTS: LEVOMENOL; BUTYLOCTYL SALICYLATE; ALKYL (C12-15) BENZOATE; TRIMETHYLPENTANEDIOL/ADIPIC ACID/GLYCERIN CROSSPOLYMER (25000 MPA.S); MEDIUM-CHAIN TRIGLYCERIDES; METHYL DIHYDROABIETATE; POLYESTER-8 (1400 MW, CYANODIPHENYLPROPENOYL CAPPED); JOJOBA OIL; TOCOPHEROL; ISOPROPYL MYRISTATE; SHEANUT OIL; PASSIFLORA EDULIS SEED OIL; GRAPE SEED OIL; SCLEROCARYA BIRREA SEED OIL

Vacation - SPF 30 Chardonnay Oil

ACTIVE INGREDIENT

Avobenzone (2.9%)

Homosalate (9.8%)

Octisalate (4.9%)

Octocrylene (9.5%)

PURPOSE

Sunscreen

Uses

• Helps prevent sunburn

• If used as directed with other sun protection measures (see Directions), decreases the risk of skin cancer and early skin aging caused by the sun.

Warnings

• For external use only
• Do not use on damaged or broken skin
• When using this product, keep out of eyes. Rinse with water to remove.

• Stop use and ask a doctor if rash occurs

• Keep out of reach of children. In case of ingestion, get medical help or contact a Poison Control Center right away.

Directions

• Apply liberally 15 minutes before sun exposure.
• Reapply: • after 80 minutes of swimming or sweating • immediately after towel drying • at least every 2 hours

• Sun Protection Measures. Spending time in the sun increases your risk of skin cancer and early skin aging. To decrease the risk, regularly use a sunscreen with a broad spectrum SPF of 15 or higher and other sun protection measures including: limit time in the sun, especially from 10 a.m. - 2 p.m. wear long-sleeve shirts, pants, hats, and sunglasses • Children under 6 months of age: ask a physician.

INACTIVE INGREDIENT

Bisabolol, Butyloctyl Salicylate, Butyrospermum Parkii (Shea) Oil, Caprylic/Capric Triglyceride, C12-15 Alkyl Benzoate, Fragrance, Isopropyl Myristrate, Methyl Dihydroabietate, Passiflora Edulis (Passionfruit) Seed Oil, Polyester-8, Sclerocarya Birrea (Marula) Seed Oil, Simmondsia Chinensis (Jojoba) Seed Oil, Tocopherol (Vitamin E),Trimethylpentanediol/Adipic Acid/Glycerin Crosspolymer, Vitis Vinifera (Chardonnay Grape) Seed Oil

Other Information

• Protect this product from excessive heat and direct sun.